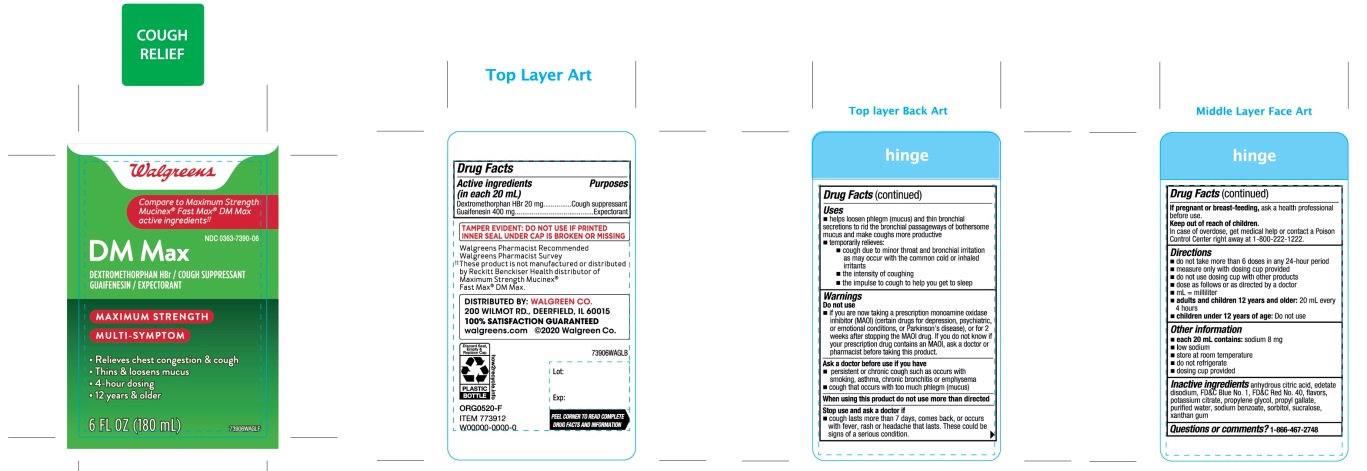 DRUG LABEL: CVS Mucus Relief DM

NDC: 69842-937 | Form: SOLUTION
Manufacturer: CVS PHARMACY
Category: otc | Type: HUMAN OTC DRUG LABEL
Date: 20251210

ACTIVE INGREDIENTS: DEXTROMETHORPHAN HYDROBROMIDE 20 mg/20 mL; GUAIFENESIN 400 mg/20 mL
INACTIVE INGREDIENTS: ANHYDROUS CITRIC ACID; EDETATE DISODIUM; FD&C BLUE NO. 1; FD&C RED NO. 40; POTASSIUM CITRATE; PROPYLENE GLYCOL; PROPYL GALLATE; WATER; SODIUM BENZOATE; SORBITOL; SUCRALOSE; XANTHAN GUM

Mucus Relief DM Maximum Strength

Drug Facts

ACTIVE INGREDIENT

PURPOSE

Active ingredients (in each 20 mL) | Purposes
Dextromethorphan HBr 20 mg | Cough suppressant
Guaifenesin 400 mg | Expectorant

Uses

- helps loosen phlegm (mucus) and thin bronchial secretions to rid the bronchial passageways of bothersome mucus and make coughs more productive
- temporarily relieves:
  - cough due to minor throat and bronchial irritation as may occur with the common cold or inhaled irritants
  - the intensity of coughing
  - the impulse to cough to help you get to sleep

Warnings

Do not use

- if you are now taking a prescription monoamine oxidase inhibitor (MAOI) (certain drugs for depression, psychiatric, or emotional conditions, or Parkinson's disease), or for 2 weeks after stopping the MAOI drug. If you do not know if your prescription drug contains an MAOI, ask a doctor or pharmacist before taking this product.

Ask a doctor before use if you have

- persistent or chronic cough such as occurs with smoking, asthma, chronic bronchitis or emphysema
- cough that occurs with too much phlegm (mucus)

When using this product

do not use more than directed

Stop use and ask a doctor if

- cough lasts more than 7 days, comes back, or occurs with fever, rash or persistent headache that lasts. These could be signs of a serious condition.

PREGNANCY OR BREAST FEEDING

If pregnant or breast-feeding,ask a health professional before use.

Keep out of reach of children.In case of overdose, get medical help or contact a Poison Control Center right away at 1-800-222-2222.

Directions

- do not take more than 6 doses in any 24-hour period
- measure only with dosing cup provided
- do not use dosing cup with other products
- dose as follows or as directed by a doctor
- mL = milliliter
- adults and children 12 years and older:20 mL every 4 hours
- children under 12 years of age:Do not use

Other information

- each 20 mL contains:sodium 8 mg
- low sodium
- store at room temperature
- do not refrigerate
- dosing cup provided

Inactive ingredients

anhydrous citric acid, edetate disodium, FD&C Blue No. 1, FD&C Red No. 40, flavors, potassium citrate , propylene glycol, propyl gallate, purified water, sodium benzoate, sorbitol, sucralose, xanthan gum.

Questions or comments?

1-866-467-2748

PRINCIPAL DISPLAY PANEL

NDC# 69842-937-06

*Compare to Maximum Strength Mucinex®Fast-Max®DM max active ingredients††

DM Max

- DEXTROMETHORPHAN HBr/COUGH SUPPRESSANT
  GUAIFENESIN 400 mg/EXPECTORANT

MAXIMUM STRENGTH

MULTI-SYMPTOM

- Relieves Chest Congestion & cough
- Thins & Loosens Mucus
- 4 Hour Dosing
- 12 years & older

For Ages 12+

6 FL OZ (180 mL)

TAMPER EVIDENT: DO NOT USE IF PRINTED INNER SEAL UNDER CAP IS BROKEN OR MISSING.

DISTRIBUTED BY:

WALGREEN CO.

200 WILMOT RD., DEERFIELD, IL 60015

100% SATISFACTION GUARANTEED

Walgreens.com © 2020 Walgreen Co.

*This product is not manufactured or distributed by Reckitt Benckiser, the distributor of Maximum Strength Mucinex®Fast -Max®DM Max.